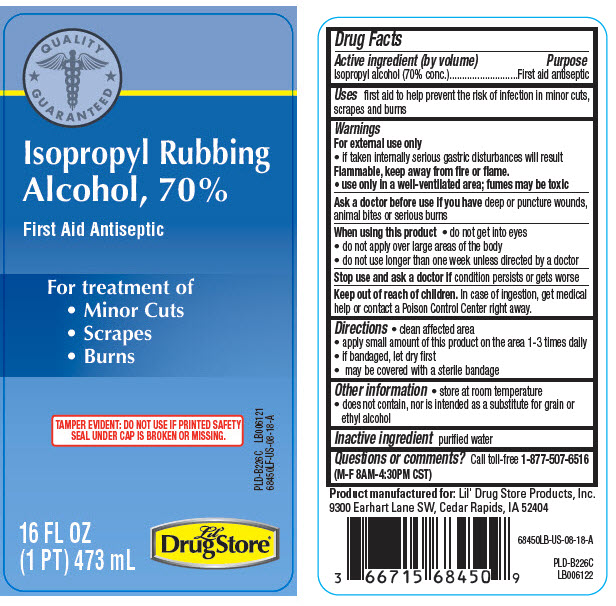 DRUG LABEL: Isopropyl Rubbing Alcohol
NDC: 66715-6845 | Form: LIQUID
Manufacturer: Lil' Drug Store Products, Inc
Category: otc | Type: HUMAN OTC DRUG LABEL
Date: 20251223

ACTIVE INGREDIENTS: ISOPROPYL ALCOHOL 70 mL/100 mL
INACTIVE INGREDIENTS: WATER

Isopropyl Rubbing Alcohol, 70%
Lil' Drug Store® Products

Drug Facts

Active ingredient (by volume)

Isopropyl alcohol (70% conc.)

Purpose

First aid antiseptic

Uses

- first aid to help prevent the risk of infection in minor cuts, scrapes and burns

Warnings

For external use only

Flammable, keep away from fire or flame.

- use only in a well-ventilated area; fumes may be toxic
- if taken internally serious gastric disturbances will result

Ask a doctor before use if you have

- deep or puncture wounds, animal bites or serious burns

When using this product

- do not get into eyes
- do not apply over large areas of the body
- do not use longer than one week unless directed by a doctor

Stop use and ask a doctor if

- condition persists or gets worse

Keep out of reach of children. In case of ingestion, get medical help or contact a Poison Control Center right away.

Directions

- clean affected area
- apply small amount of this product on the area 1-3 times daily
- if bandaged, let dry first
- may be covered with a sterile bandage

Other information

- store at room temperature
- does not contain, nor is intended as a substitute for grain or ethyl alcohol

Inactive ingredient

purified water

Questions or comments?

Call toll-free 1-877-507-6516
(M-F 8AM-4:30PM CST)

PRINCIPAL DISPLAY PANEL - 473 mL Bottle Label

QUALITY
GUARANTEED

Isopropyl Rubbing
Alcohol, 70%

First Aid Antiseptic

For treatment of

- Minor Cuts
- Scrapes
- Burns

TAMPER EVIDENT: DO NOT USE IF PRINTED SAFETY
SEAL UNDER CAP IS BROKEN OR MISSING

16 FL OZ
(1 PT) 473 mL

Lil'
DrugStore®

PLD-B226C LB006121
68450LF-US-08-18-A